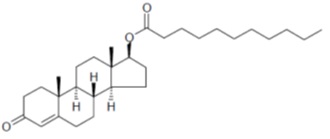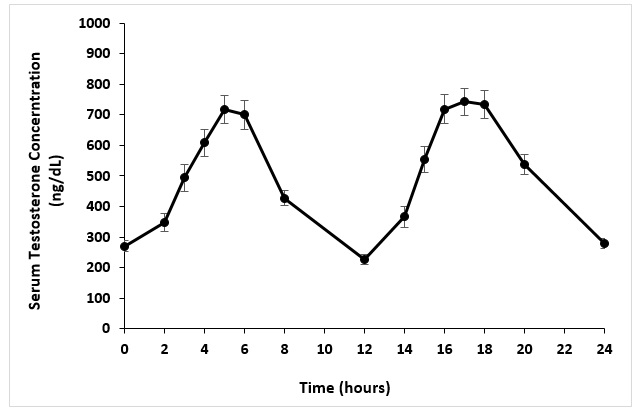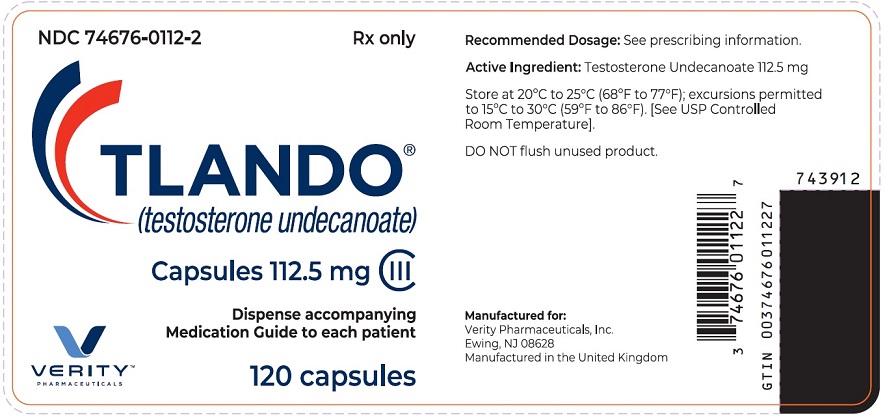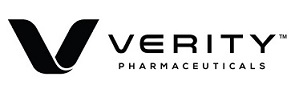 DRUG LABEL: Tlando
NDC: 74676-0112 | Form: CAPSULE, LIQUID FILLED
Manufacturer: Verity Pharmaceuticals Inc.
Category: prescription | Type: HUMAN PRESCRIPTION DRUG LABEL
Date: 20250701
DEA Schedule: CIII

ACTIVE INGREDIENTS: TESTOSTERONE UNDECANOATE 112.5 mg/1 1
INACTIVE INGREDIENTS: POLYOXYL 40 HYDROGENATED CASTOR OIL; GLYCERYL MONOLINOLEATE; GLYCERIN; TITANIUM DIOXIDE; POLYETHYLENE GLYCOL 8000; ASCORBYL PALMITATE; FERROSOFERRIC OXIDE; AMMONIA; PROPYLENE GLYCOL; shellac

HIGHLIGHTS OF PRESCRIBING INFORMATION

These highlights do not include all the information needed to use TLANDO® safely and effectively. See full prescribing information for TLANDO.
TLANDO (testosterone undecanoate) capsules, for oral use, CIII
Initial U.S. Approval: 1953

RECENT MAJOR CHANGES SECTION

Boxed Warnings, Blood Pressure Increases | Removed 07/2025
Indications and Usage, Limitations of Use (1) | 07/2025
Contraindications, Men with “age related hypogonadism” (4) | Removed 07/2025
Warnings and Precautions, Venous Thromboembolism (5.2) | 07/2025
Warnings and Precautions, Blood Pressure Increases (5.4) | 07/2025
Warnings and Precautions, Cardiovascular Risk (5.4) | Removed 07/2025

1 INDICATIONS AND USAGE

TLANDO is an androgen indicated for testosterone replacement therapy in adult males for conditions associated with a deficiency or absence of endogenous testosterone (1).

Limitations of Use

- Safety and efficacy of TLANDO in males less than 18 years old have not been established (1).
- Safety and efficacy of TLANDO in men with “age-related hypogonadism” have not been established (1).

2 DOSAGE AND ADMINISTRATION

- Prior to initiating TLANDO, confirm the diagnosis of hypogonadism by ensuring that serum testosterone concentrations have been measured in the morning on at least two separate days and that these serum testosterone concentrations are below the normal range (2.2).
- Recommended dosage is 225 mg orally twice daily with food (2.3).
- Monitor serum testosterone after initiating TLANDO to determine if TLANDO should be continued or discontinued (2.3).

3 DOSAGE FORMS AND STRENGTHS

Capsules: 112.5 mg (3)

4 CONTRAINDICATIONS

- Carcinoma of the breast or known or suspected carcinoma of the prostate (4)
- Women who are pregnant. Testosterone may cause fetal harm (4, 5.6, 8.1)
- Hypersensitivity to TLANDO or any of its ingredients (4)

5 WARNINGS AND PRECAUTIONS

- Polycythemia: Monitor hematocrit approximately every 3 months during the first year after beginning TLANDO and then every 6 months thereafter during treatment. Discontinue TLANDO if necessary (5.1).
- Venous thromboembolism (VTE): VTE, including deep vein thrombosis (DVT) and pulmonary embolism (PE) have been reported in patients using testosterone products. Discontinue TLANDO if VTE is suspected and initiate appropriate workup and management (5.2).
- Worsening of Benign Prostatic Hyperplasia (BPH) and Potential Risk of Prostate Cancer: Monitor patients with benign prostatic hyperplasia (BPH) for worsening of signs and symptoms of BPH. Evaluate patients for prostate cancer, including monitoring prostate specific antigen (PSA) prior to initiating and during treatment with androgens (5.3)
- Blood Pressure Increases: TLANDO can increase blood pressure, which can increase cardiovascular risk over time. Measure blood pressure periodically. Not recommended for use in men with uncontrolled hypertension (5.4)
- Abuse of Testosterone and Monitoring of Serum Testosterone: If testosterone use at doses higher than recommended for the approved indication and in combination with other anabolic androgenic steroids is suspected, check serum testosterone concentration (5.5).
- Potential for Adverse Effects on Spermatogenesis: TLANDO may cause azoospermia (5.7, 8.3).
- Edema: Edema, with or without congestive heart failure (CHF) may occur in patients with preexisting cardiac, renal, or hepatic disease. Discontinue TLANDO and initiate appropriate workup (5.9).
- Sleep Apnea: TLANDO may potentiate sleep apnea in those with risk factors (5.10).
- Lipid Changes: Testosterone may affect serum lipid profile. Monitor patient lipid concentrations; if necessary, adjust dosage of lipid lowering drug(s) or discontinue TLANDO (5.12).
- Increases in Prolactin: Monitor serum prolactin levels prior to initiation of TLANDO and 3 to 4 months after starting TLANDO. Discontinue TLANDO if serum prolactin levels remain elevated (5.15).

6 ADVERSE REACTIONS

Most common adverse reactions (incidence ≥ 2%): increased blood prolactin, hypertension, increased hematocrit, upper respiratory tract infection, weight increased, headache, and musculoskeletal pain (6.1).

To report SUSPECTED ADVERSE REACTIONS, contact Verity Pharma at 1-844-837-4891 or FDA at 1-800-FDA-1088 or www.fda.gov/medwatch.

7 DRUG INTERACTIONS

- Insulin: In patients with diabetes, concomitant use with TLANDO may decrease blood glucose and insulin requirements (7.1).
- Oral Anticoagulants: Concomitant use with TLANDO may cause changes in anticoagulant activity. Monitor International Normalized Ratio and prothrombin time frequently (7.2).
- Corticosteroids: Concomitant use with TLANDO may result in increased fluid retention. Use with caution, particularly in patients with cardiac, renal, or hepatic disease (7.3).
- Drugs that May Also Increase Blood Pressure: Concomitant use with TLANDO may lead to additional increases in blood pressure (7.4).

8 USE IN SPECIFIC POPULATIONS

Geriatric Patients: Geriatric patients treated with androgens may also be at risk for worsening of signs and symptoms of BPH and hypertension (8.5).

FULL PRESCRIBING INFORMATION

1 INDICATIONS AND USAGE

TLANDO is indicated for testosterone replacement therapy in adult males for conditions associated with a deficiency or absence of endogenous testosterone:

- Primary hypogonadism (congenital or acquired): testicular failure due to conditions such as cryptorchidism, bilateral torsion, orchitis, vanishing testis syndrome, orchiectomy, Klinefelter's syndrome, chemotherapy, or toxic damage from alcohol or heavy metals. These men usually have low serum testosterone concentrations and gonadotropins (follicle stimulating hormone (FSH), luteinizing hormone (LH)) above the normal range [see Dosage and Administration (2.2)].
- Hypogonadotropic hypogonadism (congenital or acquired): gonadotropin or luteinizing hormone-releasing hormone (LHRH) deficiency or pituitary-hypothalamic injury from tumors, trauma, or radiation. These men have low testosterone serum concentrations but have gonadotropins in the normal or low range [see Dosage and Administration (2.2)].

Limitations of Use

- Safety and efficacy of TLANDO in males less than 18 years old have not been established [see Use in Specific Populations (8.4)].
- Safety and efficacy of TLANDO in men with “age-related hypogonadism” (also referred to as “late-onset hypogonadism”) have not been established [see Use in Specific Populations (8.5)].

2 DOSAGE AND ADMINISTRATION

2.1 Important Dosage Information

TLANDO is not substitutable with other oral testosterone undecanoate products.

2.2 Confirmation of Hypogonadism Before Initiation of TLANDO

Prior to initiating TLANDO, confirm the diagnosis of hypogonadism by ensuring that serum testosterone concentrations have been measured in the morning on at least two separate days and that these serum testosterone concentrations are below the normal range.

2.3 Recommended Dosage

The recommended dosage of TLANDO is 225 mg (taken as two 112.5 mg capsules), orally twice daily, once in the morning and once in the evening. Take with food.

Monitoring for Continued Use or Discontinuation

Monitor serum testosterone (8 to 9 hours after the morning dose) 3 to 4 weeks after initiating TLANDO, and periodically thereafter. Based on serum testosterone measurements, determine if TLANDO should be continued or discontinued:

- Serum testosterone 300 - 1080 ng/dL: continue TLANDO
- Serum testosterone < 300 ng/dL: discontinue TLANDO
- Serum testosterone > 1080 ng/dL: discontinue TLANDO

3 DOSAGE FORMS AND STRENGTHS

Capsules: 112.5 mg, white opaque body imprinted with “112” in black ink and grey opaque cap, banded with a colorless gelatin band.

4 CONTRAINDICATIONS

TLANDO is contraindicated in:

- Patients with carcinoma of the breast or known or suspected carcinoma of the prostate [see Warnings and Precautions (5.3)].
- Women who are pregnant. Testosterone can cause virilization of the female fetus when administered to a pregnant woman [see Use in Specific Populations (8.1)].
- Known hypersensitivity to testosterone undecanoate or any of TLANDO’s ingredients [see Description (11)].

5 WARNINGS AND PRECAUTIONS

5.1 Polycythemia

Increases in hematocrit levels, reflective of increases in red blood cell mass, may require discontinuation of TLANDO. Check hematocrit prior to initiating TLANDO. Evaluate hematocrit approximately every 3 months during the first year of treatment, and then every 6 months thereafter while the patient is taking TLANDO. If hematocrit becomes elevated, stop TLANDO until hematocrit decreases to an acceptable concentration. If TLANDO is restarted and again causes hematocrit to become elevated, stop TLANDO permanently. An increase in red blood cell mass may increase the risk of thromboembolic events [see Warnings and Precautions (5.2)].

5.2 Venous Thromboembolism

There have been post marketing reports of venous thromboembolic events, including deep vein thrombosis (DVT) and pulmonary embolism (PE), in patients using testosterone replacement products such as TLANDO.

In the Testosterone Replacement therapy for Assessment of long-term Vascular Events and efficacy ResponSE in hypogonadal men (TRAVERSE) Study, a randomized, double-blind, placebo-controlled, cardiovascular (CV) outcomes study, compared to placebo, topical testosterone gel was associated with a numerically higher incidence of VTE (1.7% vs 1.2%) which included DVT (0.6% vs 0.5%) and PE events (0.9% vs 0.5%) [see Adverse Reactions (6.1)].

Evaluate patients who report symptoms of pain, edema, warmth, and erythema in the lower extremity for DVT and those who present with acute shortness of breath for PE. If a venous thromboembolic event is suspected, discontinue TLANDO and initiate appropriate workup and management [see Adverse Reactions (6.2)].

5.3 Worsening of Benign Prostatic Hyperplasia (BPH) and Potential Risk of Prostate Cancer

- Patients with BPH treated with androgens are at an increased risk for worsening of signs and symptoms of BPH. Monitor patients with BPH for worsening signs and symptoms.
- Patients treated with androgens may be at increased risk for prostate cancer. Evaluate patients for prostate cancer, including measurement of prostate specific antigen (PSA), prior to initiating and during treatment with androgens [see Contraindications (4)].

5.4 Blood Pressure Increases

TLANDO can increase blood pressure. Based on ambulatory blood pressure monitoring in Study 18-001, TLANDO increased mean systolic/diastolic BP by 4.3/1.4 mmHg from baseline after 4 months of treatment.In patients with hypertension on antihypertensive therapy, TLANDO increased the mean systolic/diastolic BP by 4.8/1.6 mm Hg from baseline. [see Adverse Reactions (6.1)]. Blood pressure increases can increase cardiovascular (CV) risk over time.

The CV risk associated with topical testosterone gel was evaluated in TRAVERSE, a randomized, double-blind, placebo-controlled, CV outcomes study in men with a history of CV disease or multiple CV risk factors. In TRAVERSE, topical testosterone gel increased mean systolic blood pressure by 1.0 mmHg from baseline to 36 months, whereas a mean decrease from baseline of 0.5 mmHg was observed in the placebo group at this timepoint, for a mean between group difference of 1.5 mmHg. However, the incidences of major adverse cardiovascular events (MACE), including cardiovascular death, non-fatal myocardial infarction [MI] and non-fatal stroke, were similar between treatment groups (7% for topical testosterone gel vs 7.3% for placebo) [See Adverse Reactions (6.1)].

Monitor BP periodically in men using TLANDO, especially men with hypertension. TLANDO is not recommended for use in patients with uncontrolled hypertension.

5.5 Abuse of Testosterone and Monitoring of Serum Testosterone Concentrations

Testosterone has been subject to abuse, typically at doses higher than recommended for the approved indication and in combination with other anabolic androgenic steroids. Anabolic androgenic steroid abuse can lead to serious cardiovascular and psychiatric adverse reactions [see Drug Abuse and Dependence (9)].

If testosterone abuse is suspected, check serum testosterone concentrations to ensure they are within therapeutic range. However, testosterone levels may be in the normal or subnormal range in men abusing synthetic testosterone derivatives. Counsel patients concerning the serious adverse reactions associated with abuse of testosterone and anabolic androgenic steroids. Conversely, consider the possibility of testosterone and anabolic androgenic steroid abuse in suspected patients who present with serious cardiovascular or psychiatric adverse events.

5.6 Not for Use in Women

Due to lack of controlled studies in women and the potential for virilizing effects, TLANDO is not indicated for use in women [see Use in Specific Populations (8.1, 8.2)].

5.7 Potential for Adverse Effects on Spermatogenesis

With large doses of exogenous androgens, including TLANDO, spermatogenesis may be suppressed through feedback inhibition of pituitary follicle-stimulating hormone (FSH) possibly leading to adverse effects on semen parameters including sperm count [see Use in Specific Populations (8.3)]. Patients should be informed of this possible risk when deciding whether to use or to continue to use TLANDO.

5.8 Hepatic Adverse Effects

Prolonged use of high doses of orally active 17-alpha-alkyl androgens (e.g., methyltestosterone) has been associated with serious hepatic adverse effects (peliosis hepatis, hepatic neoplasms, cholestatic hepatitis, and jaundice). Peliosis hepatis can be a life-threatening or fatal complication. Long-term therapy with intramuscular testosterone enanthate has produced multiple hepatic adenomas. TLANDO is not a 17 alpha-alkyl androgen and is not known to produce hepatic adverse effects associated with 17-alpha-alkyl androgens.
Nonetheless, patients should be instructed to report any signs or symptoms of hepatic dysfunction (e.g., jaundice). If these occur, promptly discontinue TLANDO while the cause is evaluated.

5.9 Edema

Androgens, including TLANDO, may promote retention of sodium and water. Edema, with or without congestive heart failure, may be a serious complication in patients with preexisting cardiac, renal, or hepatic disease [see Adverse Reactions (6.1)]. In addition to discontinuation of the drug, appropriate work up and management of edema may be required.

5.10 Sleep Apnea

The treatment of hypogonadal men with testosterone products may potentiate sleep apnea in some patients, especially those with risk factors such as obesity or chronic lung diseases.

5.11 Gynecomastia

Gynecomastia may develop and persist in patients being treated for hypogonadism.

5.12 Lipid Changes

Changes in serum lipid profile may require dose adjustment of lipid lowering drugs or discontinuation of testosterone therapy. Monitor the lipid profile periodically after starting testosterone therapy.

5.13 Hypercalcemia

Androgens, including TLANDO, should be used with caution in cancer patients at risk of hypercalcemia (and associated hypercalciuria). Monitor serum calcium concentrations periodically in these patients.

5.14 Decreased Thyroxine-binding Globulin

Androgens, including TLANDO, may decrease concentrations of thyroxin-binding globulins, resulting in decreased total T4 serum concentrations and increased resin uptake of triiodothyronine (T3) and thyroxine (T4). Free thyroid hormone concentrations remain unchanged, however, and there is no clinical evidence of thyroid dysfunction.

5.15 Increases in Prolactin

Increases in serum prolactin have been reported in patients treated with TLANDO in clinical trials. Evaluate serum prolactin levels prior to initiating treatment with TLANDO. Re-evaluate serum prolactin levels 3 to 4 months after starting treatment. If serum prolactin remains elevated, discontinue TLANDO [see Adverse Reactions (6.1)].

6 ADVERSE REACTIONS

The following clinically significant adverse reactions are discussed elsewhere in the labeling:

- Polycythemia [see Warnings and Precautions (5.1)]
- Venous Thromboembolism [see Warnings and Precautions (5.2)]
- Worsening of Benign Prostatic Hyperplasia (BPH) and Potential Risk of Prostate Cancer [see Warnings and Precautions (5.3)]
- Blood Pressure Increases [see Warnings and Precautions (5.4)]
- Hepatic Adverse Effects [see Warnings and Precautions (5.8)]
- Edema [see Warnings and Precautions (5.9)]
- Sleep Apnea [see Warnings and Precautions (5.10)]
- Gynecomastia [see Warnings and Precautions (5.11)]
- Lipid Changes [see Warnings and Precautions (5.12)]
- Hypercalcemia [see Warnings and Precautions (5.13)]
- Decreased Thyroxine-binding Globulin [see Warnings and Precautions (5.14)]
- Increases in Prolactin [see Warnings and Precautions (5.15)]

6.1 Clinical Trial Experience

Because clinical trials are conducted under widely varying conditions, adverse reaction rates observed in the clinical trials of a drug cannot be directly compared to rates in the clinical trials of another drug and may not reflect the rates observed in practice.

The safety of TLANDO 225 mg twice daily, without dose titration, was evaluated in 233 hypogonadal males during two clinical studies: Study LPCN 1021-18-001 (18-001) and Study LPCN 1021-16-002 (16-002) [see Clinical Studies (14)].

In Study 18-001, an uncontrolled ambulatory blood pressure monitoring (ABPM) study, 138 hypogonadal males were treated with TLANDO 225 mg twice daily with morning and evening meals for approximately four months. Patients had a median age of 54 years (range 26-75), 79% were White, 18% were Black, and 2% were Asian. In 138 hypogonadal male patients, 70% (n=96) were obese (BMI≥30 kg/m^2), 24% (n=33) reported a history of type 2 diabetes, and 48% (n=66) reported a history of hypertension.

Table 1 summarizes adverse reactions (>2%) reported in patients receiving TLANDO in Study 18-001.

Table 1. Adverse Reactions ≥ 2% in Patients Receiving TLANDO in Study 18-001
Adverse Reaction | Overall (N=138); n (%)
Hypertension | 7 (5.1)
Hematocrit increased | 6 (4.3)
Upper respiratory tract infection | 5 (3.6)

Four of the 138 patients (2.9%) in Study 18-001 reported adverse reactions that led to premature discontinuation from the study, including dizziness (n=1), weight increased (n=1), insomnia (n=1), and hypertension (n=2).

In Study 16-002, 95 hypogonadal males were treated with TLANDO 225 mg twice daily with morning and evening meals for approximately 24 days. The dose of TLANDO was not titrated. Patients had a median age of 56 years (range 29-74), 81% were White, 16% were Black, 2% were mixed race, and 1% were Asian; 26% were Hispanic. In 95 hypogonadal male patients, 70% (n=66) were obese (BMI≥30 kg/m^2), 23% (n=22) reported a history of type 2 diabetes, and 50% (n=47) reported a history of hypertension.

Table 2 summarized adverse reactions (>2%) reported during Study 16-002 in patients receiving TLANDO.

Table 2. Adverse Reactions ≥2% in Patients Receiving TLANDO in Study 16-002
Adverse Reaction | Overall (N=95); n (%)
Blood prolactin increased | 6 (6.3)
Weight increased | 2 (2.1)
Headache | 2 (2.1)
Musculoskeletal pain | 2 (2.1)

One of the 95 patients (1.1%) in the 24-day study reported an adverse reaction (gastric ulcer hemorrhage) that led to premature discontinuation from the study.

Blood Pressure Increases

In Study 18-001 24-hour ambulatory blood pressure monitoring (ABPM) was conducted in 138 male patients, 126 of whom completed the study. ABPM was conducted at 2 distinct 24-hour time periods: at baseline and following approximately 16 weeks of treatment with TLANDO. A total of 123 patients had acceptable 24-hour ABPM recordings at both time periods. In that group, the mean change in systolic BP from Baseline to End of Study was + 4.3 mmHg (95% CI 2.1, 6.5) and the mean change in diastolic BP was 1.4 mmHg (95% CI 0.5, 2.3). In patients with a history of hypertension at baseline, the mean ABPM systolic and diastolic blood pressure increased by 4.8 mmHg (95% CI 1.0, 8.5) and 1.6 mmHg (95% CI 0.1, 3.0), respectively (n=60). In patients with no history of hypertension at baseline systolic and diastolic blood pressure increased by 3.9 mmHg (95% CI 0.9, 6.8) and 1.2 mmHg (95% CI -0.1, 2.5), respectively (n =63).

2 patients (1.4 %) in the TLANDO safety set (n=138) either started new antihypertensive medications (n=2) or had their antihypertensive medication regimen adjusted (n=0) during Study 18-001.

Of the 138 patients in Study 18-001 who used TLANDO, 7 patients (5.1%) were reported to have either an adverse reaction of hypertension (7 patients, 5.1%) or increased blood pressure (0 patients, 0.0%).

Cardiovascular Outcomes

TRAVERSE was a randomized, double-blind, cardiovascular outcomes study to assess the cardiovascular (CV) safety of topical testosterone gel compared to placebo in 5198 hypogonadal men aged 45 to 80 years with a history of CV disease or with multiple CV risk factors. The primary outcome was the incidence of the composite endpoint of major adverse cardiovascular events (MACE), consisting of CV death, non-fatal myocardial infarction (MI), and non-fatal stroke.

The mean duration of therapy was approximately 22 months. The mean duration of follow-up was 33 months. Approximately 61% of all patients discontinued topical testosterone gel or placebo therapy.

The mean patient age (±SD) was 63.3 (7.9) years, with 2452 patients aged 65 years or more (47%), 2847 (about 55%) patients had pre-existing cardiovascular disease, whereas 2357 patients (about 45%) had an elevated cardiovascular risk at baseline, and mean BMI was 35 kg/m^2. Approximately 80% of patients were White, 17% were Black, and 3% were of other races or ethnic groups. Approximately 69%, 84%, and 93% had diabetes mellitus, hyperlipidemia, and hypertension, respectively.

The mean serum testosterone concentration at baseline in patients receiving topical testosterone gel was 220.4 ng/dL (n=2596). The mean serum testosterone concentrations at 12 months, 24 months, 36 months, and 48 months in patients receiving topical testosterone gel were 440.5 ng/dL (n=1683), 420.9 ng/dl (n=1125), 428.7 ng/dL (n=731), and 365.2 ng/dL (n=220), respectively.

For patients treated with topical testosterone gel, the incidence of MACE was 7.0% (n=182 events) and for those receiving placebo, the incidence of MACE was 7.3% (n=190 events). The study demonstrated non-inferiority of topical testosterone gel versus placebo because the upper bound of 95% CI was less than the pre-specified risk margin, of 1.5 for MACE (Hazard Ratio 0.96 [95% CI: 0.78, 1.17]).

Additional Adverse Reactions Reported in TRAVERSE

Additional adverse reactions reported in TRAVERSE at an incidence rate >2% in either treatment group and greater in topical testosterone gel versus placebo included: nonfatal arrythmias warranting intervention (5.2% vs 3.3%), atrial fibrillation (3.5% vs 2.4%), acute kidney injury (2.3% vs 1.5%) and bone fracture (3.5% vs 2.5%). For the adverse reaction of bone fracture, each event was adjudicated by clinical review.

Increases in Hematocrit

Increases in hematocrit were reported in 6 of the 138 patients (4.3%) in Study 18-001. None of these increases led to premature discontinuation of TLANDO.

Increases in Prolactin

Increases in serum prolactin were reported in 6 (6.3%) of the 95 patients in the 24-day clinical study. The mean increase from baseline in serum prolactin was 7.0 ng/mL (n=93). The 4-month clinical study did not assess serum prolactin concentrations after the screening visit.

6.2 Postmarketing Experience

The following adverse reactions have been identified during post-approval use of testosterone replacement products. Because these reactions are reported voluntarily from a population of uncertain size, it is not always possible to reliably estimate their frequency or establish a causal relationship to drug exposure.

Cardiovascular Disorders: myocardial infarction, stroke

Vascular Disorders: venous thromboembolism

7 DRUG INTERACTIONS

7.1 Insulin

Changes in insulin sensitivity or glycemic control may occur in patients treated with androgens. In diabetic patients, the metabolic effects of androgens may decrease blood glucose and, therefore, insulin requirements.

7.2 Oral Anticoagulants

Changes in anticoagulant activity may be seen with androgens. Frequent monitoring of INR and prothrombin time may be necessary in patients taking anticoagulants, especially at the initiation and termination of androgen therapy.

7.3 Corticosteroids

The concurrent use of testosterone with corticosteroids may result in increased fluid retention and should be monitored cautiously, particularly in patients with cardiac, renal or hepatic disease.

7.4 Drugs that May Also Increase Blood Pressure

Some prescription drugs and nonprescription analgesic and cold medications can increase blood pressure. Concomitant administration of these medications with TLANDO may lead to additional increases in blood pressure [see Warnings and Precautions (5.4)].

8 USE IN SPECIFIC POPULATIONS

8.1 Pregnancy

Risk Summary

TLANDO is contraindicated in pregnant women and not indicated for use in females [see Contraindications (4)]. Testosterone is teratogenic and may cause fetal harm when administered to a pregnant woman based on data from animal studies (see Data) and its mechanism of action [see Clinical Pharmacology (12.1)]. Exposure of a female fetus to androgens may result in varying degrees of virilization. In animal developmental studies, exposure to testosterone in utero resulted in hormonal and behavioral changes in offspring and structural impairments of reproductive tissues in female and male offspring. These studies did not meet current standards for nonclinical development toxicity studies.

Data

Animal Data

In developmental studies conducted in rats, rabbits, pigs, sheep and rhesus monkeys, pregnant animals received intramuscular injection of testosterone during the period of organogenesis. Testosterone treatment at doses that were comparable to those used for testosterone replacement therapy resulted in structural impairments in both female and male offspring. Structural impairments observed in females included increased anogenital distance, phallus development, empty scrotum, no external vagina, intrauterine growth retardation, reduced ovarian reserve, and increased ovarian follicular recruitment. Structural impairments seen in male offspring included increased testicular weight, larger seminal tubular lumen diameter, and higher frequency of occluded tubule lumen. Increased pituitary weight was seen in both sexes.

Testosterone exposure in utero also resulted in hormonal and behavioral changes in offspring. Hypertension was observed in pregnant females and offspring in rats exposed to doses approximately twice those used for testosterone replacement therapy.

8.2 Lactation

Risk Summary

TLANDO is not indicated for use in females.

8.3 Females and Males of Reproductive Potential

Infertility

Males

During treatment with large doses of exogenous androgens, including TLANDO, spermatogenesis may be suppressed through feedback inhibition of the hypothalamic-pituitary-testicular axis [see Warnings and Precautions (5.8)]. Reduced fertility is observed in some men taking testosterone replacement therapy. The impact on fertility may be irreversible. Testicular atrophy, subfertility, and infertility have also been reported in men who abuse anabolic androgenic steroids [see Drug Abuse and Dependence (9.2)].

8.4 Pediatric Use

The safety and effectiveness of TLANDO in pediatric patients less than 18 years old have not been established. Improper use may result in acceleration of bone age and premature closure of epiphyses.

8.5 Geriatric Use

There have not been sufficient numbers of geriatric patients in controlled clinical studies with TLANDO to determine whether efficacy or safety in those over 65 years of age differs from younger subjects. Of the 95 patients enrolled in Study 16-002, the 24-day major safety and effectiveness study utilizing TLANDO, 16 (16.8%) were over 65 years of age. Additionally, there is insufficient long-term safety data in geriatric patients utilizing TLANDO to assess the potentially increased risk of cardiovascular disease and prostate cancer.

Geriatric patients treated with androgens may also be at risk for worsening of signs and symptoms of BPH and hypertension [see Warnings and Precautions (5.3 and 5.4)].

9 DRUG ABUSE AND DEPENDENCE

9.1 Controlled Substance

TLANDO contains testosterone undecanoate, a schedule III controlled substance.

9.2 Abuse

Drug abuse is intentional non-therapeutic use of a drug, even once, for its rewarding psychological and physiological effects. Abuse and misuse of testosterone are seen in male and female adults and adolescents. Testosterone, often in combination with other anabolic androgenic steroids (AAS), and not obtained by prescription through a pharmacy, may be abused by athletes and bodybuilders. There have been reports of misuse by men taking higher doses of legally obtained testosterone than prescribed and continuing testosterone despite adverse events or against medical advice.

Abuse-Related Adverse Reactions

Serious adverse reactions have been reported in individuals who abuse anabolic androgenic steroids and include cardiac arrest, myocardial infarction, hypertrophic cardiomyopathy, congestive heart failure, cerebrovascular accident, hepatotoxicity, and serious psychiatric manifestations, including major depression, mania, paranoia, psychosis, delusions, hallucinations, hostility and aggression.

The following adverse reactions have also been reported in men: transient ischemic attacks, convulsions, hypomania, irritability, dyslipidemias, testicular atrophy, subfertility, and infertility.

The following additional adverse reactions have been reported in women: hirsutism, virilization, deepening of voice, clitoral enlargement, breast atrophy, male-pattern baldness, and menstrual irregularities.

The following adverse reactions have been reported in male and female adolescents: premature closure of bony epiphyses with termination of growth, and precocious puberty.

Because these reactions are reported voluntarily from a population of uncertain size and may include abuse of other agents, it is not always possible to reliably estimate their frequency or establish a causal relationship to drug exposure.

9.3 Dependence

Behaviors Associated with Addiction

Continued abuse of testosterone and other anabolic steroids, leading to addiction is characterized by the following behaviors:

- Taking greater dosages than prescribed
- Continued drug use despite medical and social problems due to drug use
- Spending significant time to obtain the drug when supplies of the drug are interrupted
- Giving a higher priority to drug use than other obligations
- Having difficulty in discontinuing the drug despite desires and attempts to do so
- Experiencing withdrawal symptoms upon abrupt discontinuation of use

Physical dependence is characterized by withdrawal symptoms after abrupt drug discontinuation or a significant dose reduction of a drug. Individuals taking supratherapeutic doses of testosterone may experience withdrawal symptoms lasting for weeks or months which include depressed mood, major depression, fatigue, craving, restlessness, irritability, anorexia, insomnia, decreased libido and hypogonadotropic hypogonadism.

Drug dependence in individuals using approved doses of testosterone for approved indications has not been documented.

10 OVERDOSAGE

There is one report of acute overdosage with use of an approved injectable testosterone product: this subject had serum testosterone levels of up to 11,400 ng/dL with a cerebrovascular accident.

Treatment of overdosage consists of discontinuation of TLANDO and appropriate symptomatic and supportive care.

11 DESCRIPTION

TLANDO (testosterone undecanoate) capsules contain 112.5 mg testosterone undecanoate, an ester of testosterone, for oral administration. Testosterone, an androgen, is formed by cleavage of the ester side chain of testosterone undecanoate.

The chemical name of testosterone undecanoate is 17β-undecanoyloxy-4-androsten-3-one. It has an empirical formula of C30H48O3 and a molecular weight of 456.7. The structural formula is:

Testosterone undecanoate is a white to off-white crystalline substance.

The inactive ingredients in TLANDO capsules are ascorbyl palmitate, glyceryl monolinoleate, polyethylene glycol 8000, and polyoxyl 40 hydrogenated castor oil. The capsule shell contains black iron oxide, gelatin, and titanium dioxide. The capsule is imprinted with black ink that contains ammonium hydroxide, black iron oxide, propylene glycol, and shellac.

12 CLINICAL PHARMACOLOGY

12.1 Mechanism of Action

Endogenous androgens, including testosterone and dihydrotestosterone (DHT), are responsible for the normal growth and development of the male sex organs and for maintenance of secondary sex characteristics. These effects include the growth and maturation of prostate, seminal vesicles, penis and scrotum; the development of male hair distribution, such as facial, pubic, chest and axillary hair; laryngeal enlargement, vocal cord thickening, alterations in body musculature and fat distribution.

Male hypogonadism, a clinical syndrome resulting from insufficient secretion of testosterone, has two main etiologies. Primary hypogonadism is caused by defects of the gonads, such as Klinefelter's Syndrome or Leydig cell aplasia, whereas secondary hypogonadism is the failure of the hypothalamus (or pituitary) to produce sufficient gonadotropins (FSH, LH).

12.2 Pharmacodynamics

There is insufficient data to characterize an exposure-response relationship or time course of pharmacodynamic response.

12.3 Pharmacokinetics

Absorption
Testosterone undecanoate is a lipophilic molecule that is primarily absorbed into the lymph system after oral administration and then released into the general blood circulation by the thoracic duct, avoiding absorption into the portal vein thereby circumventing first-pass metabolism in the liver. Testosterone undecanoate is converted to testosterone following absorption.

Following administration of 225 mg of TLANDO in ninety-five hypogonadal males, maximum serum testosterone concentrations were observed at a median (Tmax) of about 5 hours. The mean maximum (Cmax) serum testosterone concentrations observed were 979 ng/dL and 989 ng/dL following the morning and evening TLANDO doses, respectively. The average serum testosterone concentrations over 24 hours (Cavg0-24h) observed following TLANDO administration was 476 ng/dL.

Figure 1 shows the mean serum total testosterone concentration-time profile for hypogonadal men (N=90) administered TLANDO.

Figure 1: Mean (±SEM) Serum Total Testosterone Concentrations (ng/dL)

Following TLANDO administration, the mean serum dihydrotestosterone (DHT) Cavg0-24h was 108 ng/dL, the mean serum testosterone undecanoate Cavg0-24h was 11,100 ng/dL and the mean serum dihydrotestosterone undecanoate Cavg0-24h was 4,700 ng/dL.

Effect of Food
Administration of TLANDO with moderate fat containing food did not significantly impact the pharmacokinetic parameters of testosterone compared to high or low fat. However, there is decrease in exposure when administered without food compared to fed conditions.

In studies with 13 to 14 hypogonadal males, mean testosterone Cmax and AUC were comparable when TLANDO was administered with food containing low, moderate or high fat amounts. Administration in fasting conditions resulted in approximately 65 % and 38% lower Cmax and AUC, respectively, compared to administration with food (high fat).

Distribution
Circulating testosterone is primarily bound in serum to sex hormone-binding globulin (SHBG) and albumin. Approximately 40% of testosterone in plasma is bound to SHBG, 2% remains unbound (free) and the rest is bound to albumin and other proteins.

Elimination
The elimination half-life of testosterone undecanoate is approximately 2 hours. Once testosterone is formed from testosterone undecanoate, there is considerable variation in the half-life of testosterone as reported in the literature, ranging from 10 to 100 minutes.

Metabolism
Testosterone undecanoate is metabolized to testosterone via ester cleavage of the undecanoate group and reduced to DHTU by 5α-reductase. Testosterone is metabolized to various 17-keto steroids. The major active metabolites of testosterone are DHT and estradiol.

Excretion
About 90% of a dose of testosterone given intramuscularly is excreted in the urine as glucuronic and sulfuric acid conjugates of testosterone and its metabolites. About 6% of a dose is excreted in the feces, mostly in the unconjugated form. Inactivation of testosterone occurs primarily in the liver.

13 NONCLINICAL TOXICOLOGY

13.1 Carcinogenesis, Mutagenesis, Impairment of Fertility

Carcinogenesis

Testosterone has been tested by subcutaneous injection and implantation in mice and rats. In mice, the implant induced cervical-uterine tumors, which metastasized in some cases. There is suggestive evidence that injection of testosterone into some strains of female mice increases their susceptibility to hepatoma. Testosterone is also known to increase the number of tumors and decrease the degree of differentiation of chemically induced carcinomas of the liver in rats.

Mutagenesis

Mutagenic effects of testosterone undecanoate were not detected in a battery of in vitro tests including bacterial mutation assays (Ames test) and chromosomal aberration tests in human lymphocytes. Testosterone undecanoate was also negative in an in vivo bone marrow micronucleus assay in rats. Testosterone was negative in the in vitro Ames and in the in vivo mouse micronucleus assays.

Impairment of Fertility

The administration of exogenous testosterone has been reported to suppress spermatogenesis in the rat, dog and non-human primates, which was reversible on cessation of the treatment.

14 CLINICAL STUDIES

The efficacy and safety of TLANDO was evaluated in Study 16-002 a multicenter, open-label, single-arm study in adult hypogonadal male patients (NCT03242590). Patients received TLANDO 225 mg, orally twice daily with food for approximately 24 days; no titration was performed to adjust the dosage.

A total of 95 hypogonadal men received a dose of TLANDO and were included in the efficacy evaluation. Patients had a median age of 56 years (range 29-74 years), 81% were White, 16% were Black, 2% were mixed race, and 1% were Asian; 26% were Hispanic.

The primary endpoint was the percentage of patients who achieved a 24-hour average serum testosterone concentration (Cavg0-24h) within the normal range of 300-1080 ng/dL on the final visit of the study.

Table 3 shows the proportion of subjects, Study 16-002, with an average serum total testosterone concentration in the normal range (300-1080 ng/dL).

Table 3: Proportion of Subjects in Study 16-002 With Average Serum Total Testosterone in the Normal Range (300-1080 ng/dL) at Day 24
Parameter | N=95
% subjects with testosterone, Cavg0-24h 300 to 1080 ng/dL | 80%
95 % Confidence Interval | (72%, 88%)

Secondary endpoints were the percentage of patients with maximum total testosterone concentration (Cmax) meeting three predetermined limits: less than or equal to 1.5 times the upper limit of the normal range (ULN) (1620 ng/dL), between 1.8 and 2.5 times ULN (1944 - 2700 ng/dL), and greater than 2.5 times ULN (2700 ng/dL).

The percentage of patients who received TLANDO and had T Cmax threshold less than or equal to 1620 ng/dL, between 1944 ng/dL and 2700 ng/dL, and greater than 2700 ng/dL at the PK visit were 82%, 5%, and 0%, respectively.

16 HOW SUPPLIED/STORAGE AND HANDLING

TLANDO capsules for oral administration are available containing 112.5 mg of testosterone undecanoate. The capsules have a white opaque body imprinted with “112” in black ink and a grey opaque cap, banded with a colorless band.

TLANDO capsules are supplied in HDPE bottles with a foil liner and a child resistant cap.

Bottles of 120 capsules: NDC 74676-0112-2.

Store at 20ºC to 25°C (68ºF to 77°F); excursions permitted to 15ºC to 30°C (59ºF to 86°F). [See USP Controlled Room Temperature].

Dispose of unused TLANDO via a take-back option. If a take-back option is unavailable, follow FDA instructions at www.fda.gov/drugdisposal.

17 PATIENT COUNSELING INFORMATION

Advise the patients to read the FDA-approved patient labeling (Medication Guide).

Polycythemia

Advise patients that TLANDO can cause an increase in hematocrit levels that may increase the risk of thromboembolic events. Advise patients about the importance of completing laboratory testing as instructed by their health care provider while on TLANDO [see Warnings and Precautions (5.1)].

Venous Thromboembolism

Advise patients that TLANDO can cause venous thromboembolism. Advise patients of the signs and symptoms of venous thromboembolism, which may include the following: lower limb pain, edema, or erythema; and dyspnea or chest pain. Advise patients to promptly report the signs and symptoms of venous thromboembolism, discontinue use of TLANDO and seek urgent medical care [see Warnings and Precautions (5.2)].

Blood Pressure Increases

Advise patients that TLANDO can increase blood pressure (BP) which can increase cardiovascular risk over time. Advise patients about the importance of monitoring BP periodically while on TLANDO. If BP increases while on TLANDO, antihypertensive medications may need to be started, added, or adjusted to control BP, or TLANDO may need to be discontinued [see Warnings and Precautions (5.4)].

Worsening of Benign Prostatic Hyperplasia (BPH) and Potential Risk of Prostate Cancer

Advise patients that TLANDO can cause increased symptoms of BPH and can increase the risk for prostate cancer. Advise patients to contact their health care provider if they have any prostate-related symptoms [see Warnings and Precautions (5.3)].

Edema

Advise patients with preexisting cardiac, renal, or hepatic disease that TLANDO can cause edema. Advise patients to notify their health care provider if edema develops or worsens [see Warnings and Precautions (5.10)].

Sleep Apnea

Advise patients that TLANDO can worsen sleep apnea especially in patients with risk factors such as obesity or chronic lung diseases [see Warnings and Precautions (5.11)].

Gynecomastia

Advise patients that TLANDO can cause gynecomastia. [see Warnings and Precautions (5.12)].

Administration Instructions

- Advise patients to take TLANDO with food [see Dosage and Administration (2.3)].

Verity Pharma Medical Affairs:
1-844-VERITY-1 (1-844-837-4891)

Manufactured for:

Manufactured for Verity Pharmaceuticals, Inc.
Ewing, NJ 08628
Manufactured in the United Kingdom

TLANDO® and its design are registered trademarks of Verity Pharmaceuticals Inc.
Verity Pharmaceuticals, Verity Pharma, and their designs are trademarks of Verity Pharmaceuticals, Inc.
© 2024 Verity Pharmaceuticals Inc. All rights reserved.

TLA-001

MEDICATION GUIDE
TLANDO® (Tee-lan-doh)
(testosterone undecanoate) capsules, for oral use CIII

What is TLANDO?
TLANDO is a prescription medicine that contains testosterone. TLANDO is used to treat adult men who have low or no testosterone due to certain medical conditions.
It is not known if TLANDO is safe or effective in children younger than 18 years old. Improper use of TLANDO may affect bone growth in children.
TLANDO is a controlled substance (CIII) because it contains testosterone that can be a target for people who abuse prescription medicines. Keep your TLANDO in a safe place to protect it. Never give your TLANDO to anyone else, even if they have the same symptoms you have. Selling or giving away this medicine may harm others and is against the law.
TLANDO is not meant for use by women.

Do not take TLANDO if you:

- have breast cancer.
- have or might have prostate cancer.
- are a woman who is pregnant. TLANDO may harm your unborn baby.
- are allergic to TLANDO or any ingredients in TLANDO. See the end of this Medication Guide for a complete list of ingredients in TLANDO.
- have low testosterone without certain medical conditions. For example, do not take TLANDO if you have low testosterone due to age.

Before you take TLANDO, tell your healthcare provider about all of your medical conditions, including if you:

- have high blood pressure or are being treated for high blood pressure.
- have heart problems.
- have high red blood cell count (hematocrit) or high hemoglobin laboratory value.
- have urinary problems due to an enlarged prostate.
- have liver or kidney problems.
- have a history of mental health illness including suicidal thoughts or actions, depression, anxiety or mood disorder.
- have problems breathing while you sleep (sleep apnea).

Tell your healthcare provider about all the medicines you take, including prescription and over-the-counter medicines, vitamins, and herbal supplements.
Using TLANDO with certain other medicines can affect each other. Especially, tell your healthcare provider if you take:

- insulin.
- medicines that decrease blood clotting (blood thinners).
- corticosteroids.
- medicines that increase blood pressure such as some cold medicines and pain medicines.

Know the medicines you take. Ask your healthcare provider or pharmacist for a list of these medicines, if you are not sure. Keep a list of them and show it to your healthcare provider and pharmacist when you get a new medicine.

How should I take TLANDO?

- Take TLANDO exactly as your healthcare provider tells you take it.
- Take TLANDO by mouth two times daily. Take 2 capsules in the morning and take 2 capsules in the evening.
- Take TLANDO with food.

What are the possible side effects of TLANDO?
TLANDO may cause serious side effects including:

- See “ What is the most important information I should know about TLANDO?”
- Increase in red blood cell count (hematocrit) or hemoglobin.
  - TLANDO increases red blood cell counts in some people. High red blood cell counts increase the risk of blood clots, strokes, and heart attacks.
  - You may need to stop TLANDO if your red blood cell count increases.
  - Your healthcare provider should check your red blood cell count and hemoglobin while you use TLANDO.
- If you already have an enlarged prostate, your signs and symptoms may worsen while using TLANDO.
  These may include:
  - increased urination at night
  - trouble starting your urine stream
  - urinating many times during the day
  - urge to go to the bathroom right away
  - a urine accident
  - inability to pass urine or weak urine flow
- Increased risk of prostate cancer. Your healthcare provider should check you for prostate cancer or any other prostate problems before you start and while you use TLANDO.
- Blood clots in the legs or lungs. Signs and symptoms of a blood clot in your leg can include pain, swelling or redness. Signs and symptoms of a blood clot in your lungs can include difficulty breathing or chest pain.
- Increase in blood pressure. TLANDO can increase your blood pressure. Increases in blood pressure can increase the risk of heart attack or stroke over time. If your blood pressure increases while on TLANDO, blood pressure medicines may need to be started. If you are taking blood pressure medicines, new blood pressure medicines may need to be added or your current blood pressure medicines may need to be adjusted to control your blood pressure. If your blood pressure cannot be controlled, TLANDO may need to be stopped. Your healthcare provider will monitor your blood pressure while you are being treated with TLANDO.
- Abuse. Testosterone can be abused, when taken at higher than prescribed doses and when used with other anabolic androgenic steroids. Abuse can cause serious heart and psychological side effects. Your healthcare provider should check you for signs of abuse before and during treatment with TLANDO.
- In large doses TLANDO may lower your sperm count.
- Liver problems. Symptoms of liver problems may include:
  - nausea or vomiting
  - yellowing of your skin or whites of your eyes
  - dark urine
  - pain on the right side of your stomach area (abdominal pain)
- Swelling of your ankles, feet, or body (edema), with or without heart failure.
- Enlarged or painful breasts.
- Breathing problems while you sleep (sleep apnea).

Call your healthcare provider right away if you have any of the serious side effects listed above.
The most common side effects of TLANDO include:

- increased prolactin in your blood
- high blood pressure
- increased red blood cell count
- common cold

- increased weight
- headache
- joint and muscle pain

Tell your healthcare provider if you have any side effect that bothers you or that does not go away.
These are not all the possible side effects of TLANDO. For more information, ask your healthcare provider or pharmacist.
Call your doctor for medical advice about side effects. You may report side effects to FDA at 1-800-FDA-1088.

How should I store TLANDO?

- Store TLANDO at room temperature between 68°F to 77°F (20°C to 25°C).
- Store TLANDO in a dry place.

Keep TLANDO and all medicines out of the reach of children.

How should I throw away (dispose of) TLANDO?

- Throw away unused TLANDO via a take-back option.
- If a take-back option is unavailable, follow FDA instructions at www.fda.gov/drugdisposal for properly throwing away medicine.

General information about the safe and effective use of TLANDO
Medicines are sometimes prescribed for purposes other than those listed in a Medication Guide. Do not use TLANDO for a condition for which it was not prescribed. Do not give TLANDO to other people, even if they have the same symptoms you have. It may harm them. You can ask your pharmacist or healthcare provider for information about TLANDO that is written for health professionals.

What are the ingredients in TLANDO?
Active ingredient: testosterone undecanoate
Inactive ingredients: ascorbyl palmitate, glyceryl monolinoleate, polyethylene glycol 8000, and polyoxyl 40 hydrogenated castor oil.
Capsule shell: contains black iron oxide, gelatin, and titanium dioxide and imprint ink (ammonium hydroxide, black iron oxide, propylene glycol, and shellac).
Manufactured for:
Verity Pharmaceuticals, Inc.
Ewing, NJ 08628
Manufactured in the United Kingdom
For more information, go to www.TLANDO.com
For all medical inquiries contact:
Verity Pharma Medical Affairs
1-844-VERITY-1 (1-844-837-4891).

This Medication Guide has been approved by the U.S. Food and Drug Administration

Issued: 07/2025

PRINCIPAL DISPLAY PANEL - 112.5 mg Bottle Label - 120 Capsules

NDC 74676-0112-2 Rx Only

TLANDO®

(testosterone undecanoate)

Capsules 112.5 mg CIII

Dispense accompanying
Medication Guide to each patient

Verity Pharmaceuticals, Inc. 120 capsules